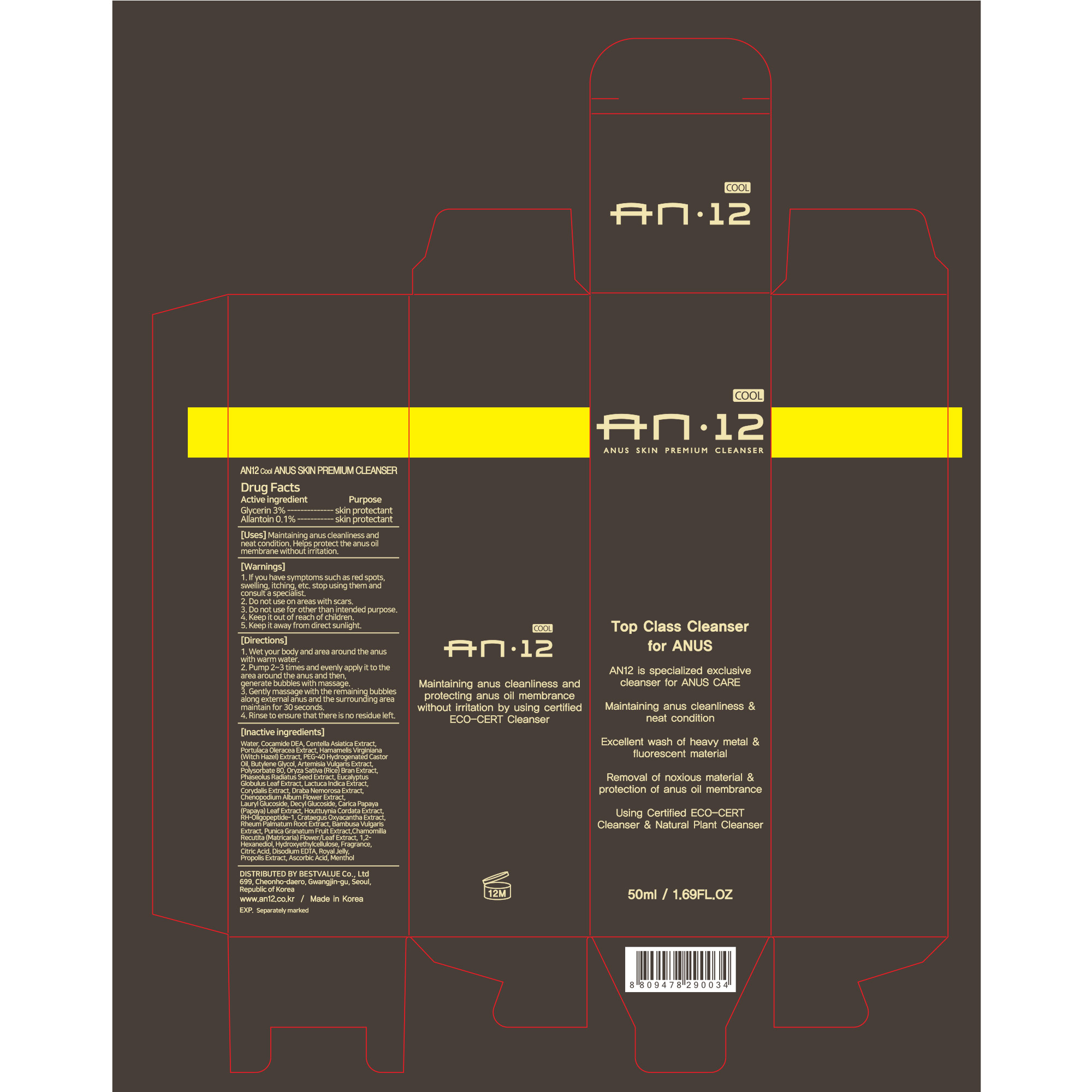 DRUG LABEL: AN12 ANUS PREMIUM CLEANSER
NDC: 82385-102 | Form: GEL
Manufacturer: BESTVALUE Co., Ltd
Category: otc | Type: HUMAN OTC DRUG LABEL
Date: 20250131

ACTIVE INGREDIENTS: GLYCERIN 3 g/100 mL; ALLANTOIN 0.1 g/100 mL
INACTIVE INGREDIENTS: EUCALYPTUS GLOBULUS LEAF; LACTUCA INDICA WHOLE; DRABA NEMOROSA WHOLE; HYDROXYETHYL CELLULOSE, UNSPECIFIED; MENTHOL; ARTEMISIA VULGARIS ROOT; POLYSORBATE 80; CENTELLA ASIATICA WHOLE; HAMAMELIS VIRGINIANA TOP; POLYOXYL 40 HYDROGENATED CASTOR OIL; MUNG BEAN; ROYAL JELLY; ASCORBIC ACID; NEPIDERMIN; RHEUM PALMATUM ROOT; BUTYLENE GLYCOL; CITRIC ACID MONOHYDRATE; LAURYL GLUCOSIDE; CARICA PAPAYA LEAF; WATER; COCO DIETHANOLAMIDE; PURSLANE; BAMBUSA VULGARIS TOP; EDETATE DISODIUM ANHYDROUS; RICE BRAN; DECYL GLUCOSIDE; CHENOPODIUM ALBUM FLOWER; HOUTTUYNIA CORDATA FLOWERING TOP; CRATAEGUS LAEVIGATA WHOLE; POMEGRANATE; MATRICARIA CHAMOMILLA FLOWERING TOP; 1,2-HEXANEDIOL; PROPOLIS WAX; CORYDALIS AMBIGUA WHOLE

82385-102 AN12 ANUS PREMIUM CLEANSER

Active Ingredients

Glycerin 3%

Allantoin 0.1%

Purpose

skin protectant

Warnings

If you have symptoms such as red spots, swelling, itching, etc. stop using them and consult a specialist.

Warnings

Do not use on areas with scars.

Warnings

Keep it out of reach of children.

Inactive Ingredients

Water, Cocamide DEA, Centella Asiatica Extract, Portulaca Oleracea Extract, Hamamelis Virginiana (Witch Hazel) Extract, PEG-40 Hydrogenated Castor Oil, Butylene Glycol, Artemisia Vulgaris Extract, Polysorbate 80, Oryza Sativa (Rice) Bran Extract, Phaseolus

Radiatus Seed Extract, Eucalyptus Globulus Leaf Extract, Lactuca Indica Extract, Corydalis Ochotensis Extract, Draba Nemorosa Extract, Chenopodium Album Flower Extract, Lauryl Glucoside, Decyl Glucoside, Carica Papaya (Papaya) Leaf Extract,

Houttuynia Cordata Extract, RH-Oligopeptide-1, Crataegus Oxyacantha Extract, Rheum Palmatum Root Extract, Bambusa Vulgaris Extract, Punica Granatum Fruit Extract, Chamomilla Recutita (Matricaria) Flower/Leaf Extract, 1,2-Hexanediol, Hydroxyethylcellulose,

Fragrance, Citric Acid, Disodium EDTA, Royal Jelly, Propolis Extract, Ascorbic Acid, Menthol

Uses

Maintaining anus cleanliness and neat condition.

Removal of noxious material such as heavy metal and fluorescent material and protection of anus oil membrance without irritation.

Directions

1. Wet your body and area around the anus with warm water.

2. Pump 2~3 times and evenly apply it to the area around the anus and then, generate bubbles with massage.

3. Gently massage with the remaining bubbles along external anus and the surrounding area and then, maintain for 30 seconds.

4. Rinse to ensure that there is no residue left.

Warnings

Do not use for other than intended purpose.